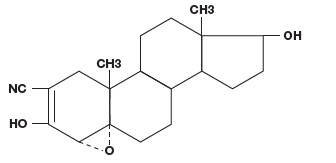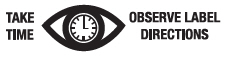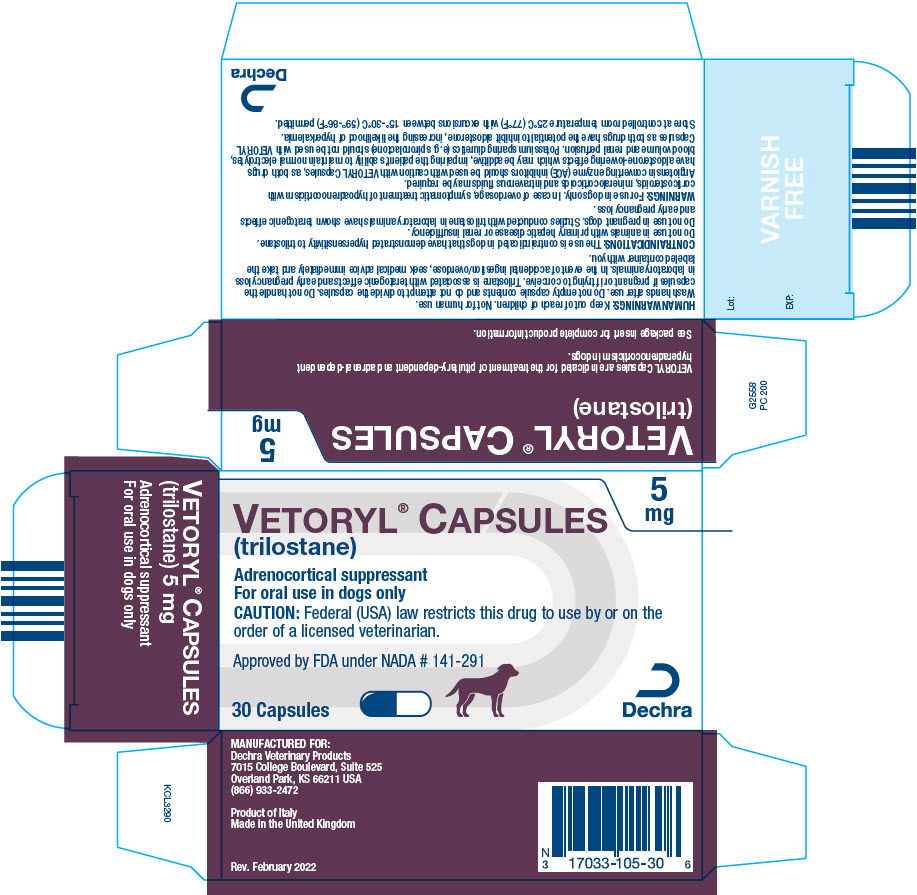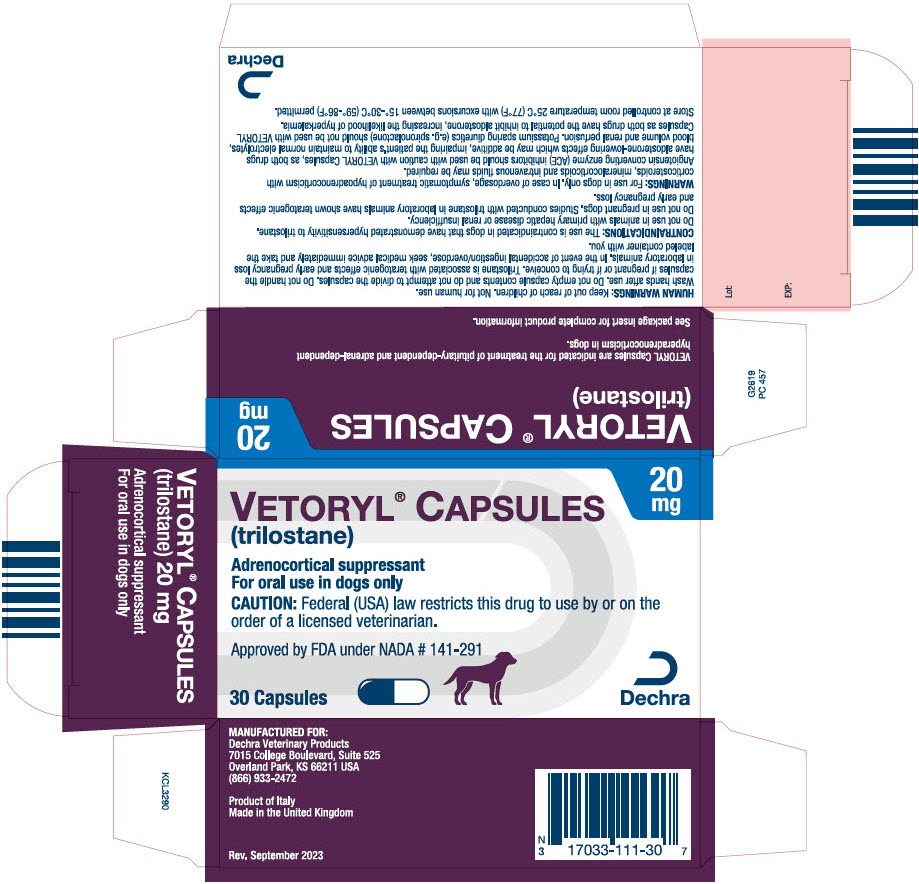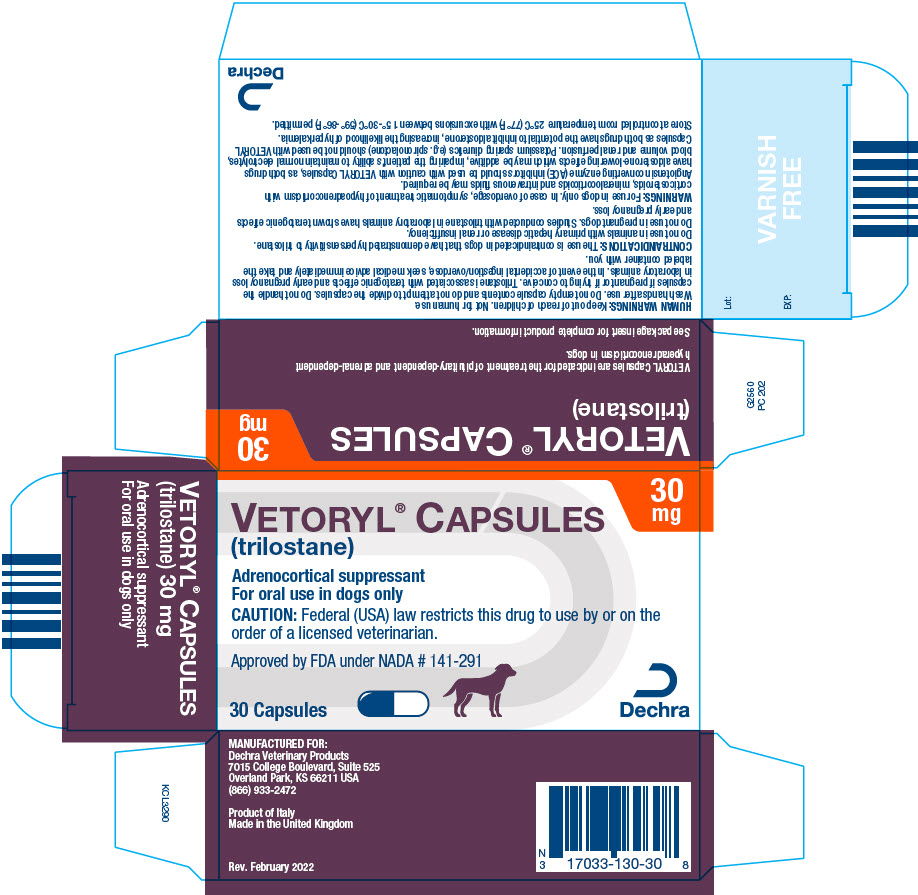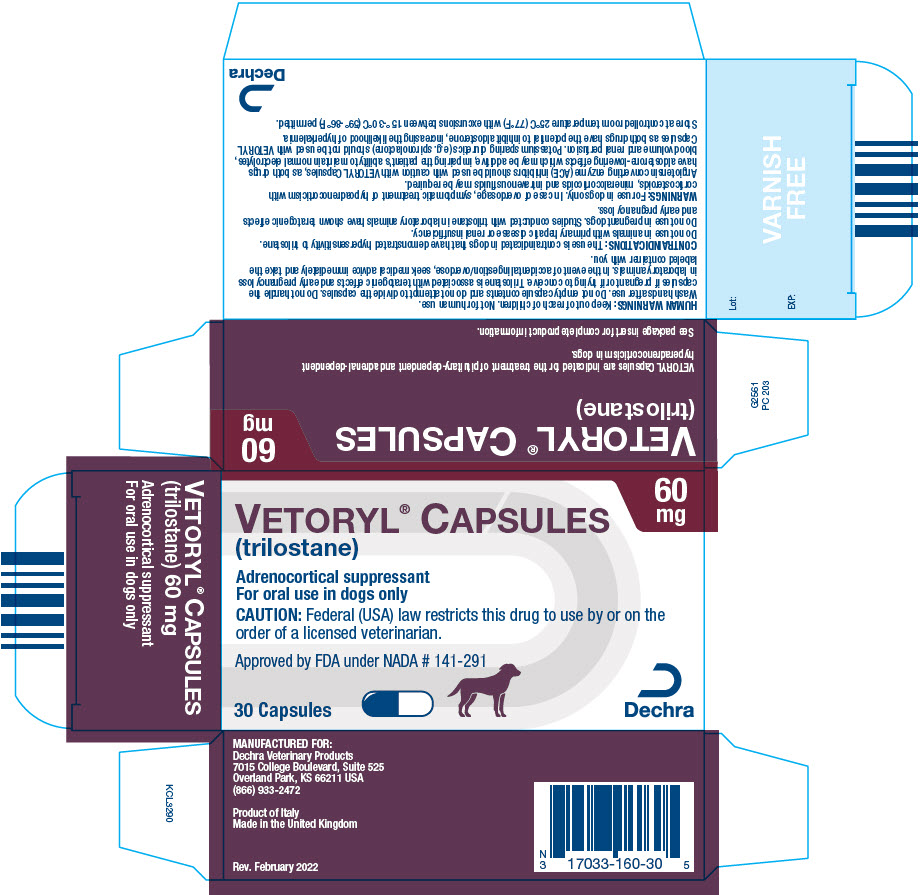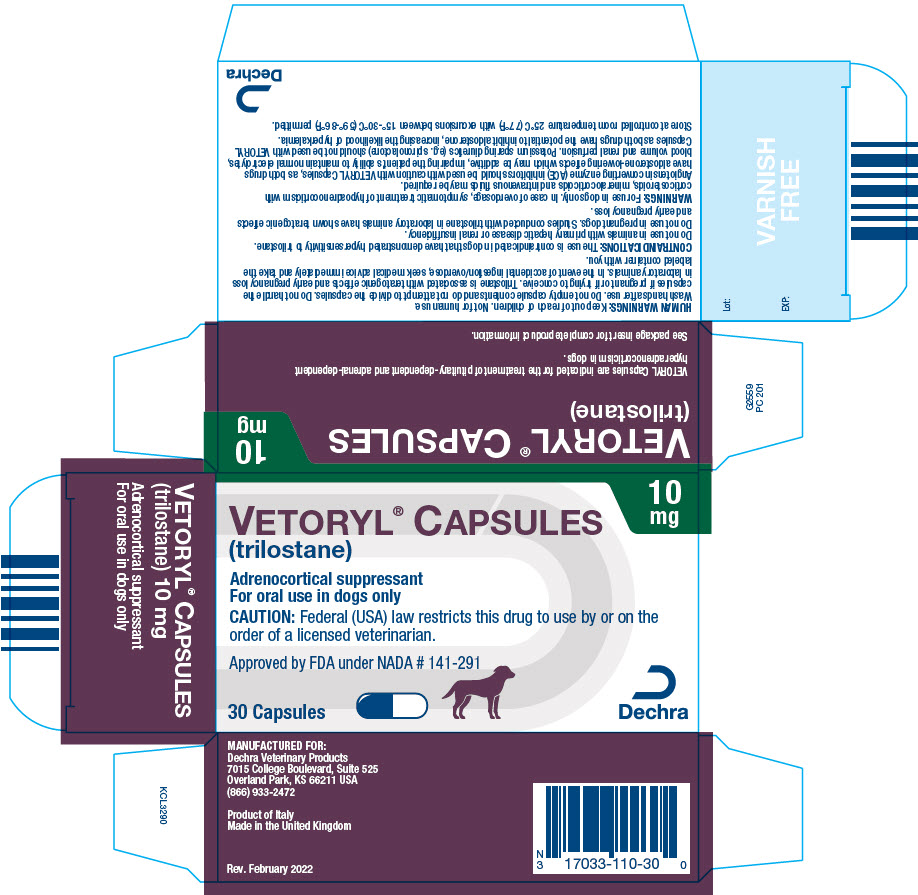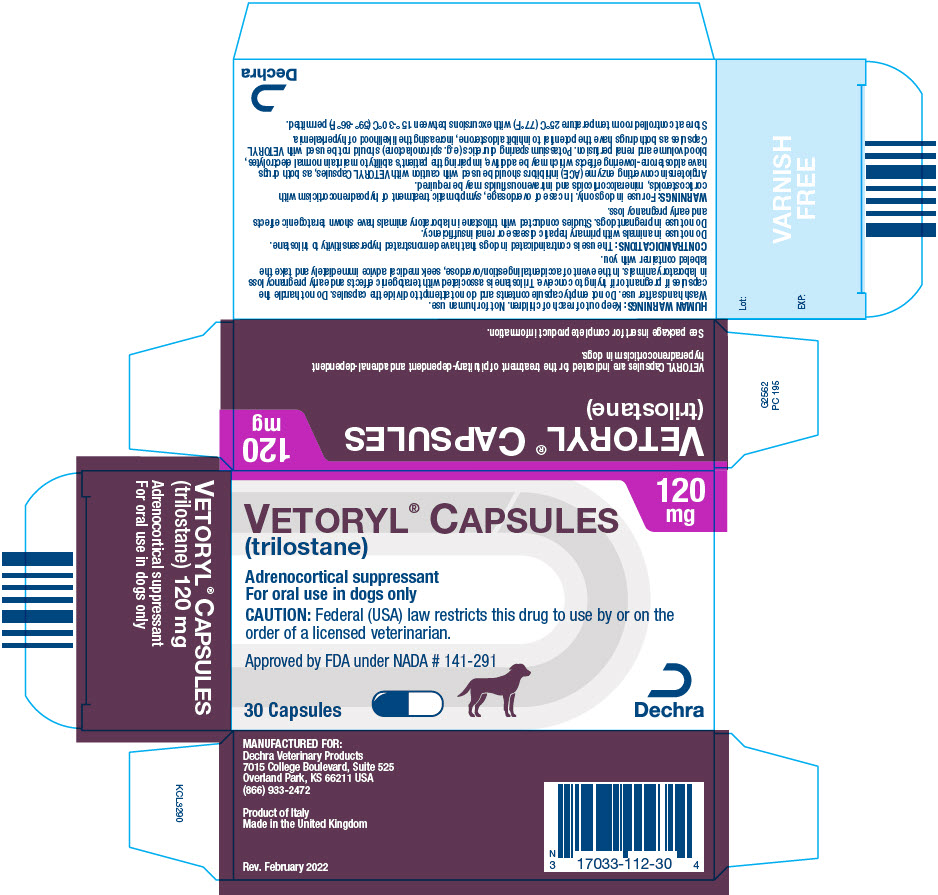 DRUG LABEL: Vetoryl
NDC: 17033-105 | Form: CAPSULE
Manufacturer: Dechra Veterinary Products
Category: animal | Type: PRESCRIPTION ANIMAL DRUG LABEL
Date: 20251216

ACTIVE INGREDIENTS: trilostane 5 mg/1 1

VETORYL® CAPSULES
(trilostane)

Adrenocortical suppressant for oral use in dogs only.

CAUTION:

Federal (USA) law restricts this drug to use by or on the order of a licensed veterinarian.

DESCRIPTION:

VETORYL Capsules are available in 6 sizes (5, 10, 20, 30, 60 and 120 mg) for oral administration based on body weight. Trilostane (4α,5α-epoxy-17β-hydroxy-3-oxoandrostane-2α-carbonitrile) is an orally active synthetic steroid analogue that selectively inhibits 3 β-hydroxysteroid dehydrogenase in the adrenal cortex, thereby inhibiting the conversion of pregnenolone to progesterone. This inhibition blocks production of glucocorticoids and to a lesser extent, mineralocorticoids and sex hormones while steroid precursor levels increase. The structural formula is:

INDICATIONS:

VETORYL Capsules are indicated for the treatment of pituitary-dependent and adrenal-dependent hyperadrenocorticism in dogs.

DOSAGE AND ADMINISTRATION:

Always provide the Client Information Sheet with prescription (see INFORMATION FOR DOG OWNERS).

1. Starting dose

The starting dose for the treatment of hyperadrenocorticism in dogs is 1-3 mg/lb (2.2-6.7 mg/kg) once a day. Start with the lowest possible dose based on body weight and available combinations of capsule sizes. VETORYL Capsules should be administered with food.

2. Action at 10-14 day evaluation (Table 1)

After approximately 10-14 days at this dose, re-examine the dog and conduct a 4-6 hour post-dosing ACTH stimulation test and serum biochemical tests (with particular attention to electrolytes, and renal and hepatic function). If physical examination is acceptable, take action according to Table 1.

Owners should be instructed to stop therapy and contact their veterinarian immediately in the event of adverse reactions such as vomiting, diarrhea, lethargy, poor/reduced appetite, weakness, collapse or any other unusual developments. If these clinical signs are observed, conduct an ACTH stimulation test and serum biochemical tests (with particular attention to electrolytes, and renal and hepatic function).

Table 1: Action at 10-14 day evaluation
Post-ACTH serum cortisol |  | Action
µg/dL | nmol/L | Action
< 1.45 | < 40 | Stop treatment. Re-start at a decreased dose
1.45 to 5.4 | 40 to 150 | Continue on same dose
> 5.4 to 9.1 | > 150 to 250 | EITHER: Continue on current dose if clinical signs are well controlled OR: Increase dose if clinical signs of hyperadrenocorticism are still evident [Combinations of capsule sizes should be used to slowly increase the once daily dose.]
> 9.1 | > 250 | Increase initial dose

3. Individual dose adjustments and close monitoring are essential

Re-examine and conduct an ACTH stimulation test and serum biochemical tests (with particular attention to electrolytes, and renal and hepatic function) 10-14 days after every dose alteration. Care must be taken during dose increases to monitor the dog's clinical signs.

Once daily administration is recommended. However, if clinical signs are not controlled for the full day, twice daily dosing may be needed. To switch from a once daily dose to a twice daily dose, the total daily dose should be divided into 2 portions given 12 hours apart. It is not necessary for the portions to be equal. If applicable, the larger dose should be administered in the morning and the smaller dose in the evening. For example, a dog receiving 90 mg would receive 60 mg in the morning, and 30 mg in evening.

4. Long term monitoring

Once an optimum dose of VETORYL Capsules has been reached, re-examine the dog at 30 days, 90 days and every 3 months thereafter. At a minimum, this monitoring should include:

- A thorough history and physical examination.
- An ACTH stimulation test (conducted 4-6 hours after VETORYL Capsule administration) - a post-ACTH stimulation test resulting in a cortisol of < 1.45 μg/dL (< 40 nmol/L), with or without electrolyte abnormalities, may precede the development of clinical signs of hypoadrenocorticism.
- Serum biochemical tests (with particular attention to electrolytes, and renal and hepatic function).

Good control is indicated by favorable clinical signs as well as post-ACTH serum cortisol of 1.45-9.1 μg/dL (40-250 nmol/L).

If the ACTH stimulation test is < 1.45 µg/dL (< 40 nmol/L) and/or if electrolyte imbalances characteristic of hypoadrenocorticism (hyperkalemia and hyponatremia) are found, VETORYL Capsules should be temporarily discontinued until recurrence of clinical signs consistent with hyperadrenocorticism and ACTH stimulation test results return to normal (1.45-9.1 µg/dL or 40-250 nmol/L).

VETORYL Capsules may then be re-introduced at a lower dose.

CONTRAINDICATIONS:

The use of VETORYL Capsules is contraindicated in dogs that have demonstrated hypersensitivity to trilostane.

Do not use VETORYL Capsules in animals with primary hepatic disease or renal insufficiency (See WARNINGS and PRECAUTIONS).

Do not use in pregnant dogs. Studies conducted with trilostane in laboratory animals have shown teratogenic effects and early pregnancy loss.

WARNINGS:

Hypoadrenocorticism can develop at any dose of VETORYL Capsules. In some cases, it may take months for adrenal function to return and some dogs never regain adequate adrenal function.

All dogs should undergo a thorough history and physical examination before initiation of therapy with VETORYL Capsules. Other conditions, such as primary hepatic and/or renal disease should be considered when the patient is exhibiting signs of illness in addition to signs of hyperadrenocorticism (e.g. vomiting, diarrhea, poor/reduced appetite, weight loss, and lethargy). Appropriate laboratory tests to establish hematological and serum biochemical baseline data prior to, and periodically during, administration of VETORYL Capsules should be considered.

Owners should be advised to discontinue therapy immediately and contact their veterinarian if signs of potential drug toxicity are observed (see INFORMATION FOR DOG OWNERS, DOSAGE AND ADMINISTRATION, PRECAUTIONS, ADVERSE REACTIONS, ANIMAL SAFETY and POST-APPROVAL EXPERIENCE).

In case of overdosage, symptomatic treatment of hypoadrenocorticism with corticosteroids, mineralocorticoids and intravenous fluids may be required.

Angiotensin converting enzyme (ACE) inhibitors should be used with caution with VETORYL Capsules, as both drugs have aldosterone-lowering effects which may be additive, impairing the patient's ability to maintain normal electrolytes, blood volume and renal perfusion. Potassium sparing diuretics (e.g. spironolactone) should not be used with VETORYL Capsules as both drugs have the potential to inhibit aldosterone, increasing the likelihood of hyperkalemia.

HUMAN WARNINGS:

Keep out of reach of children. Not for human use.

Wash hands after use. Do not empty capsule contents and do not attempt to divide the capsules. Do not handle the capsules if pregnant or if trying to conceive. Trilostane is associated with teratogenic effects and early pregnancy loss in laboratory animals. In the event of accidental ingestion/overdose, seek medical advice immediately and take the labeled container with you.

PRECAUTIONS:

Mitotane (o,p'-DDD) treatment will reduce adrenal function. Experience in foreign markets suggests that when mitotane therapy is stopped, an interval of at least one month should elapse before the introduction of VETORYL Capsules. It is important to wait for both the recurrence of clinical signs consistent with hyperadrenocorticism, and a post-ACTH cortisol level of > 9.1 μg/dL (> 250 nmol/L) before treatment with VETORYL Capsules is initiated. Close monitoring of adrenal function is advised, as dogs previously treated with mitotane may be more responsive to the effects of VETORYL Capsules.

The use of VETORYL Capsules will not affect the adrenal tumor itself. Adrenalectomy should be considered as an option for cases that are good surgical candidates. The safe use of this drug has not been evaluated in lactating dogs and males intended for breeding.

ADVERSE REACTIONS:

The most common adverse reactions reported are poor/reduced appetite, vomiting, lethargy/dullness, diarrhea, and weakness. Occasionally, more serious reactions, including severe depression, hemorrhagic diarrhea, collapse, hypoadrenocortical crisis or adrenal necrosis/rupture may occur, and may result in death.

In a US field study with 107 dogs, adrenal necrosis/rupture (two dogs) and hypoadrenocorticism (two dogs) were the most severe adverse reactions in the study. One dog died suddenly of adrenal necrosis, approximately one week after starting trilostane therapy. One dog developed an adrenal rupture, believed to be secondary to adrenal necrosis, approximately six weeks after starting trilostane therapy. This dog responded to trilostane discontinuation and supportive care.

Two dogs developed hypoadrenocorticism during the study. These two dogs had clinical signs consistent with hypoadrenocorticism (lethargy, anorexia, collapse) and post-ACTH cortisol levels ≤ 0.3 μg/dL. Both dogs responded to trilostane discontinuation and supportive care, and one dog required continued treatment for hypoadrenocorticism (glucocorticoids and mineralocorticoids) after the acute presentation.

Additional adverse reactions were observed in 93 dogs. The most common of these included diarrhea (31 dogs), lethargy (30 dogs), inappetence/anorexia (27 dogs), vomiting (28 dogs), musculoskeletal signs (lameness, worsening of degenerative joint disease) (25 dogs), urinary tract infection (UTI)/hematuria (17 dogs), shaking/shivering (10 dogs), otitis externa (8 dogs), respiratory signs (coughing, congestion) (7 dogs), and skin/coat abnormality (seborrhea, pruritus) (8 dogs).

Five dogs died or were euthanized during the study (one dog secondary to adrenal necrosis, discussed above, two dogs due to progression of pre-existing congestive heart failure, one dog due to progressive central nervous system signs, and one dog due to cognitive decline leading to inappropriate elimination). In addition to the two dogs with adrenal necrosis/rupture and the two dogs with hypoadrenocorticism, an additional four dogs were removed from the study as a result of possible trilostane-related adverse reactions, including collapse, lethargy, inappetence, and trembling. Complete blood counts conducted pre- and post-treatment revealed a statistically significant (p <0.005) reduction in red cell variables (HCT, HGB, and RBC), but the mean values remained within the normal range. Additionally, approximately 10% of the dogs had elevated BUN values (≥ 40 mg/dL) in the absence of concurrent creatinine elevations. In general, these dogs were clinically normal at the time of the elevated BUN.

In a long term follow-up study of dogs in the US effectiveness study, the adverse reactions were similar to the short term study. Vomiting, diarrhea and general gastrointestinal signs were most commonly observed. Lethargy, inappetence/anorexia, heart murmur or cardiopulmonary signs, inappropriate urination/incontinence, urinary tract infections or genitourinary disease, and neurological signs were reported. Included in the US follow-up study were 14 deaths, three of which were possibly related to trilostane. Eleven dogs died or were euthanized during the study for a variety of conditions considered to be unrelated to or to have an unknown relationship with administration of trilostane.

In two UK field studies with 75 dogs, the most common adverse reactions seen were vomiting, lethargy, diarrhea/loose stools, and anorexia. Other adverse reactions included: nocturia, corneal ulcer, cough, persistent estrus, vaginal discharge and vulvar swelling in a spayed female, hypoadrenocorticism, electrolyte imbalance (elevated potassium with or without decreased sodium), collapse and seizure, shaking, muscle tremors, constipation, scratching, weight gain, and weight loss. One dog died of congestive heart failure and another died of pulmonary thromboembolism. Three dogs were euthanized during the study. Two dogs had renal failure and another had worsening arthritis and deterioration of appetite.

In a long term follow-up of dogs included in the UK field studies, the following adverse reactions were seen: hypoadrenocortical episode (including syncope, tremor, weakness, and vomiting), hypoadrenocortical crisis or renal failure (including azotemia, vomiting, dehydration, and collapse), chronic intermittent vaginal discharge, hemorrhagic diarrhea, occasional vomiting, and distal limb edema. Signs of hypoadrenocorticism were usually reversible after withdrawal of the drug, but may be permanent. One dog discontinued VETORYL Capsules and continued to have hypoadrenocorticism when evaluated a year later. Included in the follow-up were reports of deaths, at least 5 of which were possibly related to use of VETORYL Capsules. These included dogs that died or were euthanized because of renal failure, hypoadrenocortical crisis, hemorrhagic diarrhea, and hemorrhagic gastroenteritis.

Foreign Market Experience: The following events were reported voluntarily during post-approval use of VETORYL Capsules in foreign markets. The most serious adverse events were death, adrenal necrosis, hypoadrenocorticism (electrolyte alterations, weakness, collapse, anorexia, lethargy, vomiting, diarrhea, and azotemia), and corticosteroid withdrawal syndrome (weakness, lethargy, anorexia, and weight loss). Additional adverse events included: renal failure, diabetes mellitus, pancreatitis, autoimmune hemolytic anemia, vomiting, diarrhea, anorexia, skin reactions (rash, erythematous skin eruptions), hind limb paresis, seizures, neurological signs from growth of macroadenomas, oral ulceration, and muscle tremors.

POST-APPROVAL EXPERIENCE:

As of June 2013, the following adverse events are based on post-approval adverse drug experience reporting. Not all adverse reactions are reported to FDA CVM. It is not always possible to reliably estimate the adverse event frequency or establish a causal relationship to product exposure using this data. The following adverse events are listed in decreasing order of reporting frequency: anorexia, lethargy/depression, vomiting, diarrhea, elevated liver enzymes, elevated potassium with or without decreased sodium, elevated BUN, decreased Na/K ratio, hypoadrenocorticism, weakness, elevated creatinine, shaking, renal insufficiency. In some cases, death has been reported as an outcome of the adverse events listed above.

To report suspected adverse events and/or obtain a copy of the SDS or for technical assistance, call Dechra Veterinary Products at (866) 933-2472.

For additional information about adverse drug experience reporting for animal drugs, contact FDA at 1-888-FDA-VETS or online at: http://www.fda.gov/reportanimalae

INFORMATION FOR DOG OWNERS:

Owners should be aware that the most common adverse reactions may include: an unexpected decrease in appetite, vomiting, diarrhea, or lethargy and should receive the Client Information Sheet with the prescription. Owners should be informed that control of hyperadrenocorticism should result in resolution of polyphagia, polyuria and polydipsia. Serious adverse reactions associated with this drug can occur without warning and in some cases result in death (see ADVERSE REACTIONS and POST-APPROVAL EXPERIENCE).

Owners should be advised to discontinue VETORYL Capsules and contact their veterinarian immediately if signs of intolerance such as vomiting, diarrhea, lethargy, poor/reduced appetite, weakness, or collapse are observed. Owners should be advised of the importance of periodic follow-up for all dogs during administration of VETORYL Capsules.

CLINICAL PHARMACOLOGY:

Trilostane absorption is enhanced by administration with food. In healthy dogs, maximal plasma levels of trilostane occur within 1.5 hours, returning to baseline levels within twelve hours, although large inter-dog variation occurs. There is no accumulation of trilostane or its metabolites over time.

EFFECTIVENESS:

Eighty-three dogs with hyperadrenocorticism were enrolled in a multi-center US field study. Additionally, 30 dogs with hyperadrenocorticism were enrolled in two UK field studies. Results from these studies demonstrated that treatment with VETORYL Capsules resulted in an improvement in clinical signs (decreased thirst, decreased frequency of urination, decreased panting, and improvement of appetite and activity). Improvement in post-ACTH cortisol levels occurred in most cases within 14 days of starting VETORYL Capsules therapy.

In these three studies, there were a total of 10 dogs diagnosed with hyperadrenocorticism due to an adrenal tumor or due to concurrent pituitary and adrenal tumors. Evaluation of these cases failed to demonstrate a difference in clinical, endocrine, or biochemical response when compared to cases of pituitary-dependent hyperadrenocorticism.

ANIMAL SAFETY:

In a laboratory study, VETORYL Capsules were administered to 8 healthy 6 month old Beagles per group at 0× (empty capsules), 1×, 3×, and 5× the maximum starting dose of 6.7 mg/kg twice daily for 90 days. Three animals in the 3× group (receiving 20.1 mg/kg twice daily) and five animals in the 5× group (receiving 33.5 mg/kg twice daily) died between Days 23 and 46. They showed one or more of the following clinical signs: decreased appetite, decreased activity, weight loss, dehydration, soft stool, slight muscle tremors, diarrhea, lateral recumbency, and staggering gait. Bloodwork showed hyponatremia, hyperkalemia, and azotemia, consistent with hypoadrenocortical crisis. Post-mortem findings included epithelial necrosis or cystic dilation of duodenal mucosal crypts, gastric mucosal or thymic hemorrhage, atrial thrombosis, pyelitis and cystitis, and inflammation of the lungs.

ACTH stimulated cortisol release was reduced in all dogs treated with VETORYL Capsules. The dogs in the 3× and 5× groups had decreased activity. The 5× dogs had less weight gain than the other groups. The 3× and 5× dogs had lower sodium, albumin, total protein, and cholesterol compared to the control dogs. The 5× dogs had lower mean corpuscular volume than the controls. There was a dose dependent increase in amylase. Post-mortem findings included dose dependent adrenal cortical hypertrophy.

STORAGE INFORMATION:

Store at controlled room temperature 25°C (77°F) with excursions between 15°-30°C (59°-86°F) permitted.

HOW SUPPLIED:

VETORYL Capsules are available in 5, 10, 20, 30, 60 and 120 mg strengths, packaged in aluminum foil blister cards of 10 capsules, with 3 cards per carton.

VETORYL Capsules 5 mg | NDC 17033-105-30
VETORYL Capsules 10 mg | NDC 17033-110-30
VETORYL Capsules 20 mg | NDC 17033-111-30
VETORYL Capsules 30 mg | NDC 17033-130-30
VETORYL Capsules 60 mg | NDC 17033-160-30
VETORYL Capsules 120 mg | NDC 17033-112-30

Approved by FDA under NADA # 141-291

Manufactured for:
Dechra Veterinary Products
7015 College Boulevard, Suite 525
Overland Park, KS 66211 USA

VETORYL is a registered trademark of Dechra Limited

F2203 Rev. February 2024

Dog Owner Information About VETORYL® Capsules (trilostane)
Adrenocortical suppressant for oral use in dogs only

VETORYL (pronounced "vet-or-ill") Capsules
Generic name: trilostane ("try-low-stain")

This summary contains important information about VETORYL Capsules. You should read this information before you start giving your dog VETORYL Capsules and review it each time the prescription is refilled.

This sheet is provided only as a summary and does not take the place of instructions from your veterinarian. Talk to your veterinarian if you do not understand any of this information or if you want to know more about VETORYL Capsules.

What are VETORYL Capsules?

VETORYL Capsules contain an adrenosuppressant drug that is used to treat hyperadrenocorticism in dogs.

VETORYL Capsules are a prescription drug for dogs.

Hyperadrenocorticism (also known as Cushing's disease) is a condition in which excess levels of the hormone cortisol are produced. Cortisol is normally released from the adrenal gland into the bloodstream at times of stress.

In dogs with hyperadrenocorticism, the level of cortisol produced is excessive and, if left untreated, becomes incapacitating.

Characteristic signs are:

- Passing large quantities of urine
- Frequent urination and possible incontinence
- Excessive drinking
- Ravenous appetite
- Lethargy or decreased activity
- Excessive panting
- Pot belly
- Thin skin
- Hair loss or recurrent skin diseases
- Muscle wasting

Your dog may not necessarily display all of these signs.

What should I talk to my veterinarian about before giving VETORYL Capsules?

Periodic follow-up and laboratory testing are important for continual safe use of VETORYL Capsules. Talk with your veterinarian about how often your dog will need to be examined.

Talk to your veterinarian about:

- What tests might be done before VETORYL Capsules are prescribed.
- How often your dog may need to be examined by your veterinarian.
- The risks and benefits of using VETORYL Capsules.

Tell your veterinarian if your dog has ever had the following medical problems:

- Liver disease
- Kidney disease

Tell your veterinarian about:

- Any other medical problems or allergies that your dog has now or has had.
- If your dog is pregnant, nursing or if you plan to breed your dog.
- Any medications your dog is taking, including over-the-counter products and nutritional supplements.

What are the possible side effects that may occur in my dog during therapy?

VETORYL Capsules, like other drugs, may cause some side effects. Serious side effects have been reported in dogs taking VETORYL Capsules. Serious side effects can occur with or without warning and result in death.

Side effects generally involve an over suppression of the adrenal glands (hypoadrenocorticism, also known as Addison's Disease). Look for the following side effects that may indicate your dog is having a problem with VETORYL Capsules or may have another medical problem:

- Depression, lethargy or decrease in activity
- Change in bowel movements (such as diarrhea or loose stools)
- Vomiting
- Stops eating or loses all interest in food
- Weakness and collapse

It is important to stop therapy and contact your veterinarian immediately if you think your dog has a medical problem or side effect from VETORYL Capsule therapy. If you have additional questions about possible side effects, talk to your veterinarian.

As VETORYL Capsules control the hyperadrenocorticism, there should be a decrease in food and water consumption to normal levels. There should also be resolution of excess urination. If, however, there is a dramatic decrease in appetite or your dog stops drinking water, it could be an indication of a side effect requiring treatment.

What kind of results can I expect when my dog is on VETORYL Capsules?

Although VETORYL Capsules ARE NOT A CURE for hyperadrenocorticism, the product can control the clinical signs:

- Response varies from dog to dog.
- Improvement can be seen in most dogs within a few weeks.
- If VETORYL Capsules are discontinued or not given as directed, excess cortisol production can resume and the signs of hyperadrenocorticism can return.

Which dogs should not take VETORYL Capsules?

Your dog should not be given VETORYL Capsules if he/she:

- Has kidney or liver disease.
- Takes certain medications. VETORYL Capsules should be used with caution with several medications used to treat heart disease (some diuretics and ACE inhibitors).
- Is pregnant.

Tell your veterinarian about all medicines you have given your dog in the past, and any medicines that you are planning to give with VETORYL Capsules. This should include other medicines that you can get without a prescription. Your veterinarian may want to check that all of your dog's medicines can be given together.

What should I know about giving VETORYL Capsules to my dog?

- VETORYL Capsules should be given according to your veterinarian's instructions. Your veterinarian will tell you the number of VETORYL Capsules that is right for your dog.
- Administer capsules with food.
- Keep out of reach of children. Not for human use.
- Do not open capsules and do not attempt to split or divide capsules.
- Wash hands after use.
- Do not handle the capsules if pregnant or trying to become pregnant. Studies in laboratory animals have produced birth defects and early pregnancy loss. In the event of accidental ingestion/overdose, seek medical advice immediately and take the labeled container with you.

What do I do in case my dog takes more than the prescribed amount of VETORYL Capsules?

Contact your veterinarian immediately if your dog takes more than the prescribed amount of VETORYL Capsules.

What else should I know about VETORYL Capsules?

This sheet provides a summary of information about VETORYL Capsules. If you have any questions or concerns about VETORYL Capsules or hyperadrenocorticism, talk to your veterinarian.

As with all prescribed medicines, VETORYL Capsules should only be given to the dog for which it was prescribed.

It is important to periodically discuss your dog's response to VETORYL Capsules at regular checkups. Your veterinarian will determine if your dog is responding as expected and if your dog should continue receiving VETORYL Capsules.

Approved by FDA under NADA # 141-291

Manufactured for:
Dechra Veterinary Products
7015 College Boulevard, Suite 525
Overland Park, KS 66211 USA

VETORYL is a registered trademark of Dechra Limited

Rev. February 2024

F2205

PRINCIPAL DISPLAY PANEL - 5 mg Capsule Blister Pack Package

5
mg

VETORYL® CAPSULES
(trilostane)

Adrenocortical suppressant
For oral use in dogs only

CAUTION: Federal (USA) law restricts this drug to use by or on the
order of a licensed veterinarian.

Approved by FDA under NADA # 141-291

30 Capsules
Dechra

PRINCIPAL DISPLAY PANEL - 10 mg Capsule Blister Pack Package

10
mg

VETORYL® CAPSULES
(trilostane)

Adrenocortical suppressant
For oral use in dogs only

CAUTION: Federal (USA) law restricts this drug to use by or on the
order of a licensed veterinarian.

Approved by FDA under NADA # 141-291

30 Capsules
Dechra

PRINCIPAL DISPLAY PANEL - 20 mg Capsule Blister Pack Package

20
mg

VETORYL® CAPSULES
(trilostane)

Adrenocortical suppressant
For oral use in dogs only

CAUTION: Federal (USA) law restricts this drug to use by or on the
order of a licensed veterinarian.

Approved by FDA under NADA # 141-291

30 Capsules
Dechra

PRINCIPAL DISPLAY PANEL - 30 mg Capsule Blister Pack Package

30
mg

VETORYL® CAPSULES
(trilostane)

Adrenocortical suppressant
For oral use in dogs only

CAUTION: Federal (USA) law restricts this drug to use by or on the
order of a licensed veterinarian.

Approved by FDA under NADA # 141-291

30 Capsules
Dechra

PRINCIPAL DISPLAY PANEL - 60 mg Capsule Blister Pack Package

60
mg

VETORYL® CAPSULES
(trilostane)

Adrenocortical suppressant
For oral use in dogs only

CAUTION: Federal (USA) law restricts this drug to use by or on the
order of a licensed veterinarian.

Approved by FDA under NADA # 141-291

30 Capsules
Dechra

PRINCIPAL DISPLAY PANEL - 120 mg Capsule Blister Pack Package

120
mg

VETORYL® CAPSULES
(trilostane)

Adrenocortical suppressant
For oral use in dogs only

CAUTION: Federal (USA) law restricts this drug to use by or on the
order of a licensed veterinarian.

Approved by FDA under NADA # 141-291

30 Capsules
Dechra